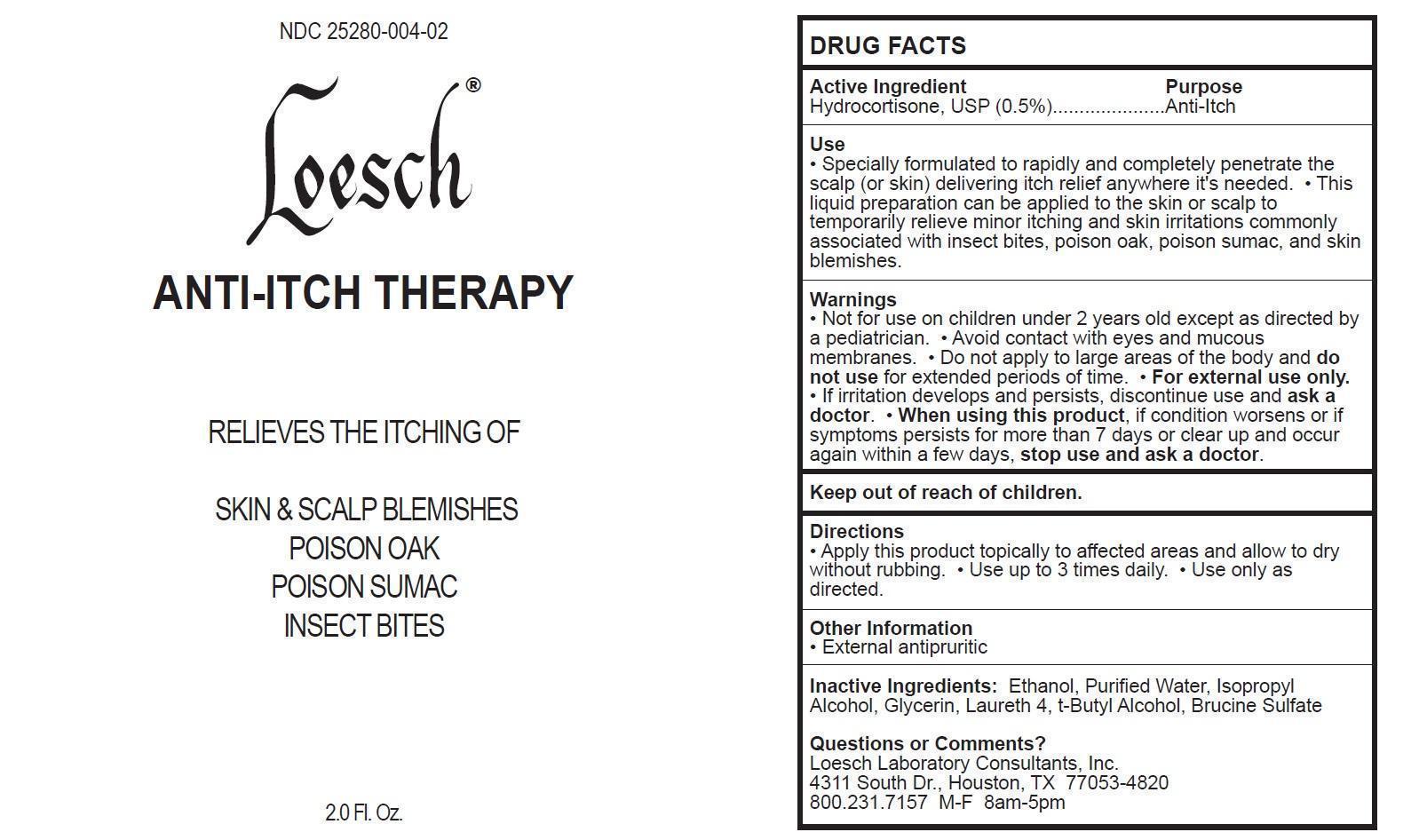 DRUG LABEL: Loesch
NDC: 25280-004 | Form: LIQUID
Manufacturer: Loesch Laboratory Consultants, Inc.
Category: otc | Type: HUMAN OTC DRUG LABEL
Date: 20140626

ACTIVE INGREDIENTS: HYDROCORTISONE 5 mg/1 mL
INACTIVE INGREDIENTS: ALCOHOL; WATER; ISOPROPYL ALCOHOL; GLYCERIN; LAURETH-4; TERT-BUTYL ALCOHOL; BRUCINE SULFATE

Loesch Anti-Itch Therapy

Active Ingredient

Hydrocortisone, USP (0.5%)

Purpose

Anti-Itch

Use

- Specially formulated to rapidly and completely penetrate the scalp (or skin) delivering itch relief anywhere it's needed.
- This liquid preparation can be applied to the skin or scalp to temporarily relieve minor itching and skin irritations commonly associated with insect bites, poison oak, poison sumac, and skin blemishes.

Warnings

- Not for use on children under 2 years old except as directed by a pediatrician.
- Avoid contact with eyes and mucous membranes.
- Do not apply to large areas of the body and do not use for extended periods of time.
- For external use only.
- If irritation develops and persists, discontinue use and ask a doctor.
- When using this product, if condition worsens or if symptoms persists for more than 7 days or clear up and occur again within a few days, stop use and ask a doctor.

Keep out of reach of children.

Directions

- Apply this product topically to affected areas and allow to dry without rubbing.
- Use up to 3 times daily.
- Use only as directed.

Other Information

- External antipruritic

Inactive Ingredients:

Ethanol, Purified Water, Isopropyl Alcohol, Glycerin, Laureth 4, t-Butyl Alcohol, Brucine Sulfate

Questions or Comments?

Loesch Laboratory Consultants, Inc.
4311 South Dr., Houston, TX 77053-4820
800.231.7157 M-F 8am-5pm

Image of 2.0 Fl. Oz. Label NDC:25280-004-02

LoeschAntiItchTherapy2oz.jpg